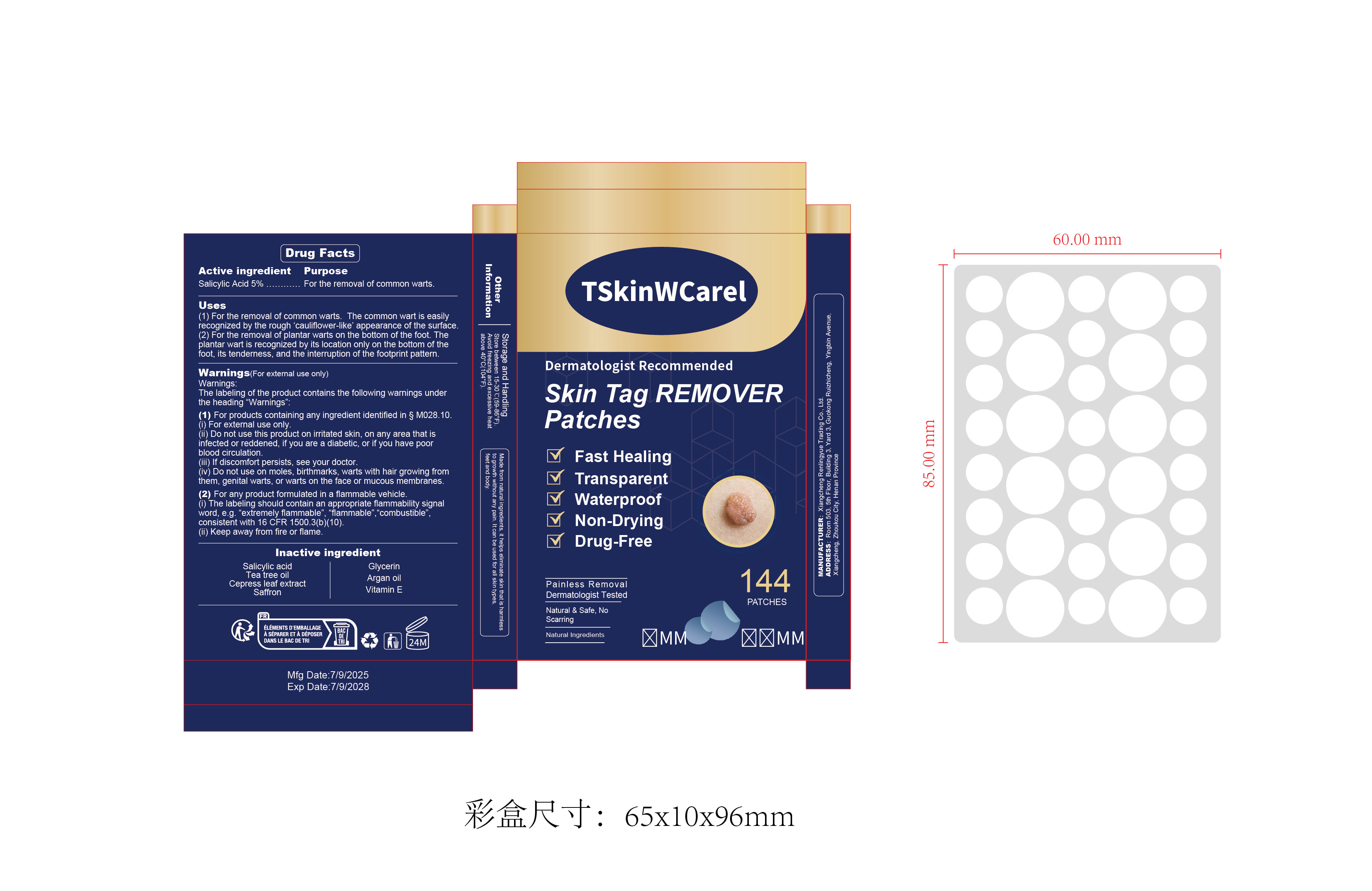 DRUG LABEL: Skin Tag Remover  Patches
NDC: 85593-006 | Form: PATCH
Manufacturer: Guangzhou ChuanMa International Trading Co.,Ltd.
Category: otc | Type: HUMAN OTC DRUG LABEL
Date: 20250813

ACTIVE INGREDIENTS: SALICYLIC ACID 5 g/100 g
INACTIVE INGREDIENTS: SAFFRON; ARGAN OIL; GLYCERIN; ALPHA-TOCOPHEROL; TEA TREE OIL; CUPRESSUS SEMPERVIRENS LEAF

ACTIVE INGREDIENT

Salicylic Acid 5%
For the removal of common warts.

KEEP OUT OF CHILDREN

PURPOSE

Fast HealingTransparentWaterproofNon-DryingDrug-Free

WARNINGS

Warnings.The labeling of the product contains the following warnings underthe heading “Warnings”
(1)For products containing any ingredient identified in S MO28.10.(i)For external use only.(ii) Do not use this product on irritated skin, on any area that isinfected or reddened, if you are a diabetic, or if you have poorblood circulation.
(iii) lf discomfort persists, see your doctor.(iv) Do not use on moles, birthmarks, warts with hair growing fromthem, genital warts, or warts on the face or mucous membranes.
(2) For any product formulated in a flammable vehicle.(i)The labeling should contain an appropriate flammability signalword, e.g.“extremely flammable",“flammable".“combustible”consistent with 16 CFR 1500.3(b)(10).(ii) Keep away from fire or flame.

DOSAGE AND ADMINISTRATION

(1)For the removal of common warts. The common wart is easily
recognized by the rough 'cauliflower-like’ appearance of the surface.

INDICATIONS AND USAGE

For the removal of plantar warts on the bottom of the foot. The
plantar wart is recognized by its location only on the bottom of the
foot, its tenderness, and the interruption of the footprint pattern.

INACTIVE INGREDIENT

Salicylic acidTea tree oilCepress leaf extractSaffron
GlycerinArgan oilVitamin E

Do not use this product on irritated skin, on any area that is
infected or reddened, if you are a diabetic, or if you have poor
blood circulation.